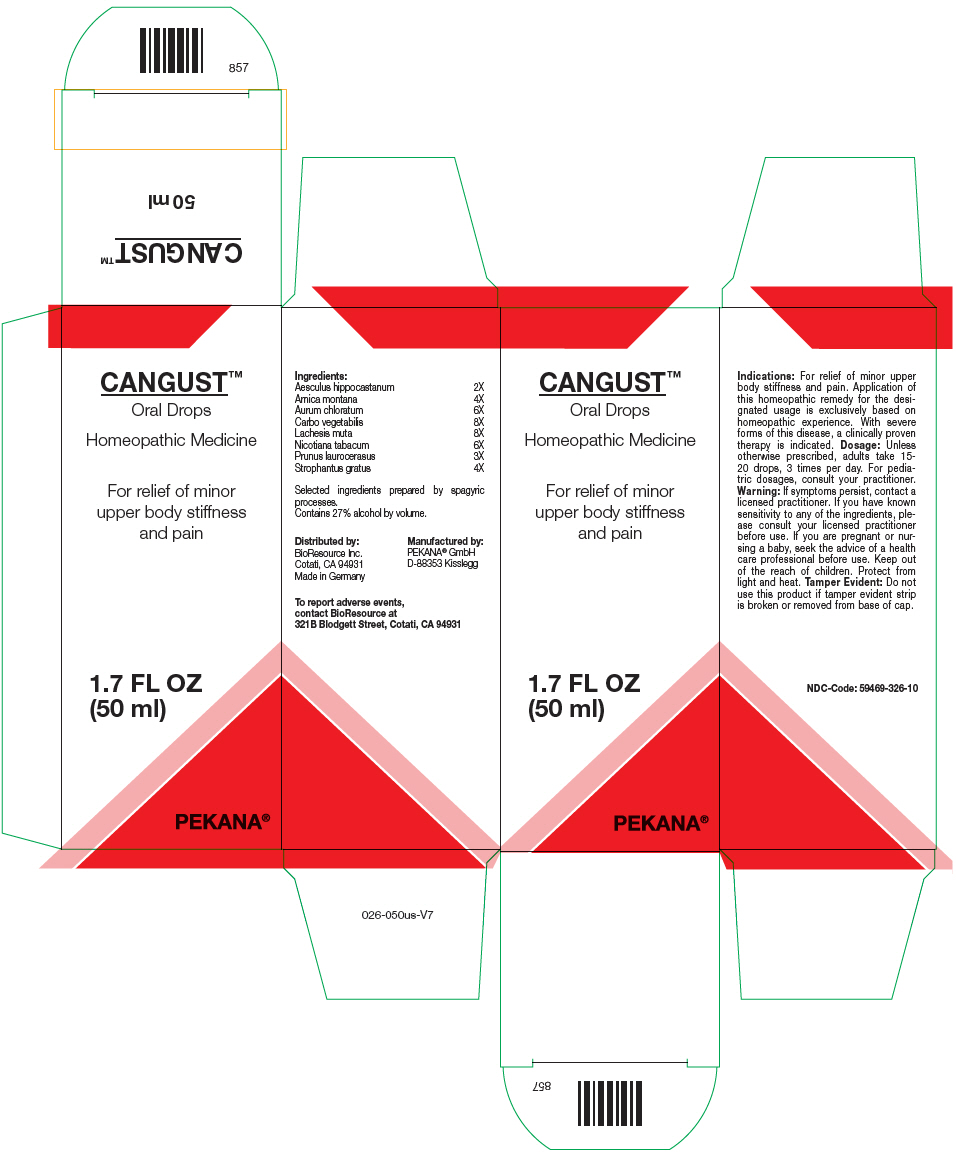 DRUG LABEL: CANGUST
NDC: 59469-326 | Form: SOLUTION/ DROPS
Manufacturer: PEKANA Naturheilmittel GmbH
Category: homeopathic | Type: HUMAN OTC DRUG LABEL
Date: 20221227

ACTIVE INGREDIENTS: HORSE CHESTNUT 2 [hp_X]/50 mL; ARNICA MONTANA ROOT 4 [hp_X]/50 mL; GOLD TRICHLORIDE 6 [hp_X]/50 mL; ACTIVATED CHARCOAL 8 [hp_X]/50 mL; LACHESIS MUTA VENOM 8 [hp_X]/50 mL; PRUNUS LAUROCERASUS LEAF 3 [hp_X]/50 mL; STROPHANTHUS GRATUS SEED 4 [hp_X]/50 mL; TOBACCO LEAF 6 [hp_X]/50 mL
INACTIVE INGREDIENTS: WATER; ALCOHOL

CANGUST™

ACTIVE INGREDIENT

Ingredients:
Aesculus hippocastanum | 2X
Arnica montana | 4X
Aurum chloratum | 6X
Carbo vegetabilis | 8X
Lachesis muta | 8X
Nicotiana tabacum | 6X
Prunus laurocerasus | 3X
Strophantus gratus | 4X

Selected ingredients prepared by spagyric processes.

INACTIVE INGREDIENT

Contains 27% alcohol by volume.

Indications

PURPOSE

For relief of minor upper body stiffness and pain. Application of this homeopathic remedy for the designated usage is exclusively based on homeopathic experience. With severe forms of this disease, a clinically proven therapy is indicated.

Dosage

Unless otherwise prescribed, adults take 15-20 drops, 3 times per day. For pediatric dosages, consult your practitioner.

Warning

If symptoms persist, contact a licensed practitioner. If you have known sensitivity to any of the ingredients, please consult your licensed practitioner before use. If you are pregnant or nursing a baby, seek the advice of a health care professional before use.

Keep out of the reach of children.

STORAGE AND HANDLING

Protect from light and heat.

Tamper Evident

Do not use this product if tamper evident strip is broken or removed from base of cap.

QUESTIONS

To report adverse events, contact BioResource at 321B Blodgett Street, Cotati, CA 94931

Distributed by:
BioResource Inc.
Cotati, CA 94931

Manufactured by:
PEKANA® GmbH
D-88353 Kisslegg

PRINCIPAL DISPLAY PANEL - 50 mL Bottle Box

CANGUST™

Oral Drops

Homeopathic Medicine

For relief of minor
upper body stiffness
and pain

1.7 FL OZ
(50 ml)

PEKANA®